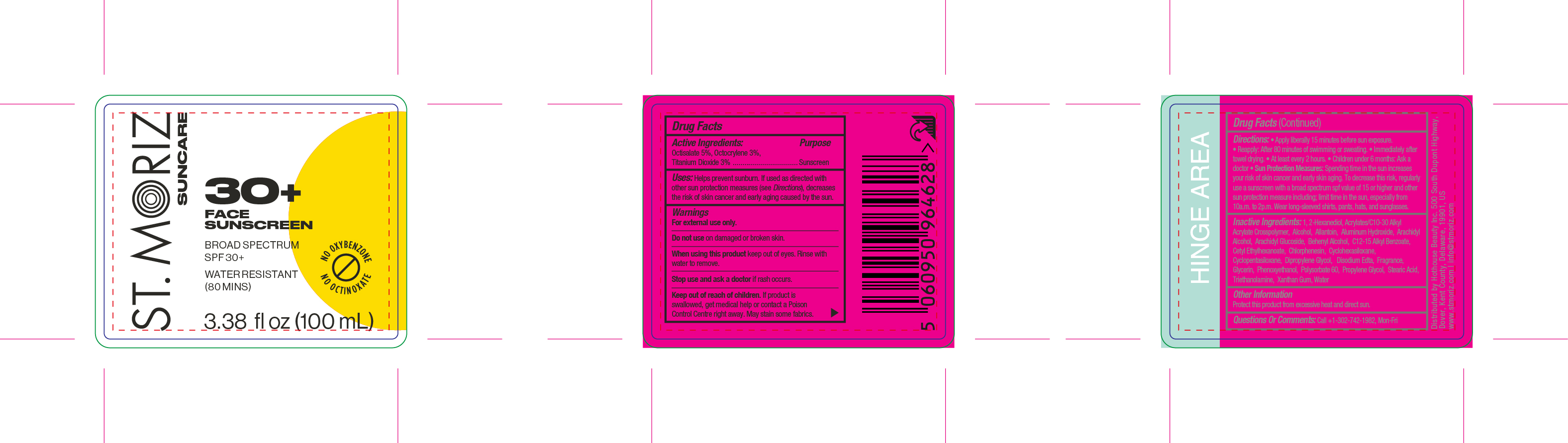 DRUG LABEL: St. Moriz Suncare 30 Face Sunscreen
NDC: 85178-2225 | Form: LOTION
Manufacturer: Hothouse Beauty Inc
Category: otc | Type: HUMAN OTC DRUG LABEL
Date: 20250120

ACTIVE INGREDIENTS: OCTOCRYLENE 30 mg/1 mL; OCTISALATE 50 mg/1 mL; TITANIUM DIOXIDE 30 mg/1 mL
INACTIVE INGREDIENTS: ARACHIDYL GLUCOSIDE; XANTHAN GUM; PROPYLENE GLYCOL; GLYCERIN; STEARIC ACID; WATER; TRIETHANOLAMINE; CYCLOPENTASILOXANE; PHENOXYETHANOL; EDETATE DISODIUM; CHLORPHENESIN; ACRYLATES/C10-30 ALKYL ACRYLATE CROSSPOLYMER (60000 MPA.S); CYCLOHEXASILOXANE; DIPROPYLENE GLYCOL; ALCOHOL; BEHENYL ALCOHOL; CETYL ETHYLHEXANOATE; 1,2-HEXANEDIOL; ALUMINUM HYDROXIDE; ARACHIDYL ALCOHOL; C12-15 ALKYL BENZOATE; POLYSORBATE 60; ALLANTOIN

St. Moriz Suncare 30+ Face Sunscreen

Active Ingredient

Active Ingredients: octocrylene 3%, octisalate 5%, Titanium Dioxide 3%

Uses

- Helps prevent sunburn
- If used as directed with other sun protection measures (see Directions) decreases risk of skin cancer and early skin aging caused by the sun

Warnings

- For external use only.
- Do not use on damaged or broken skin
- When using this product [bullet] keep out of eyes. Rinse with water to remove.
- Stop use and ask a doctor if [bullet] rash or irritation develops and lasts.
- Keep out of reach of children, If product is swallowed, get medical help or contact poison control centre right away.
- To ensure compatibility, we recommend patch testing before first use. In the unlikely event of a negative reaction, discontinue use and consult your medical practitioner.

Do not use on damaged or broken skin

When using this product

keep out of eyes. Rinse with water to remove.

Keep out of reach of children. If product is swallowed, get medical help or contact Poison Control Center right away.

Directions

- Apply generously 15 minutes before sun exposure”
- Reapply [bullet] after 80 minutes of swimming or sweating [bullet] immediately after towel drying [bullet] at least every 2 hours
- Children under 6 months of age: Ask a doctor
- Sun Protection Measures.Spending time in the sun increases your risk of skin cancer and early skin aging. To decrease this risk, regularly use a sunscreen with a Broad Spectrum SPF value of 15 or higher and other sun protection measures including:  limit time in the sun, especially from 10 a.m. - 2 p.m.  wear long-sleeved shirts, pants, hats, and sunglasses

Inactive ingredients

1,2-Hexanediol, Acrylates/C10-30 Alkyl Acrylate Crosspolymer, Alcohol, Allantoin, Aluminum Hydroxide, Arachidyl Alcohol, Arachidyl Glucoside, Behenyl Alcohol, C12-15 Alkyl Benzoate, Cetyl Ethylhexanoate, Chlorphenesin, Cyclohexasiloxane, Cyclopentasiloxane, Dipropylene Glycol, Disodium Edta, Fragrance, Glycerin, Phenoxyethanol, Polysorbate 60, Propylene Glycol, Stearic Acid, Triethanolamine, Xanthan Gum, Water

Other Information

Protect the product in this container from excessive heat and direct sun. Store below 30 degrees celcius.

Uses

Helps prevent sunburn.

St. Moriz Suncare 30+ Face Sunscreen

NDC85178-2225-1

100 mL / 3.38 fl oz

Principal Display Panel and information panel primary container: